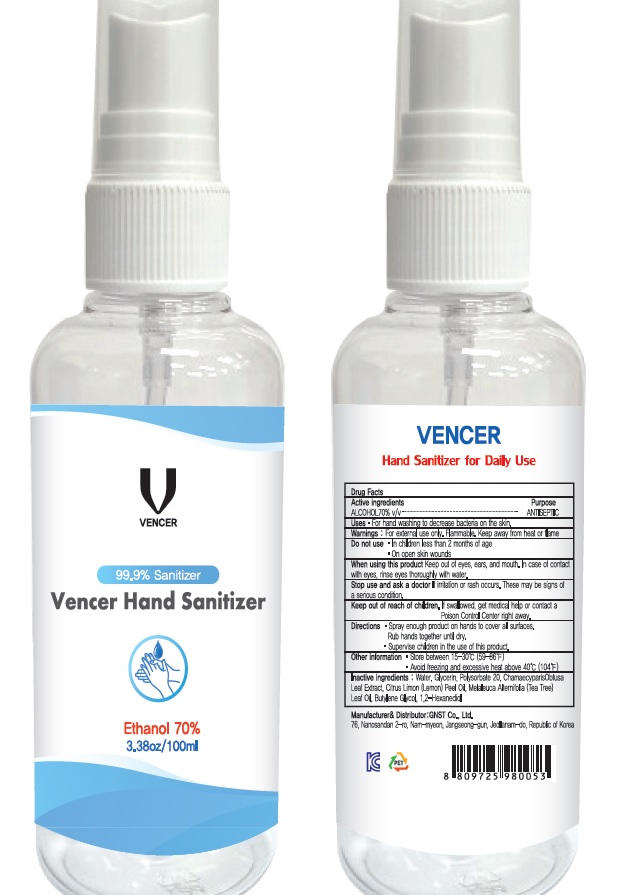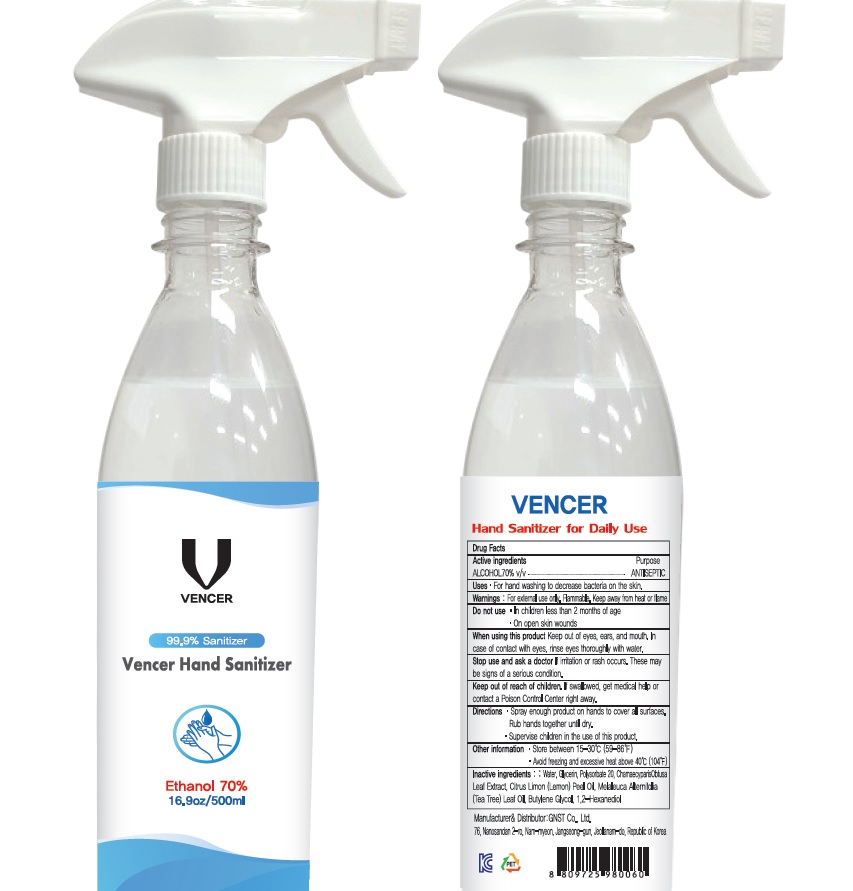 DRUG LABEL: VENCER Hand Sanitizer
NDC: 78454-020 | Form: SPRAY
Manufacturer: GNST Co.,Ltd.
Category: otc | Type: HUMAN OTC DRUG LABEL
Date: 20200602

ACTIVE INGREDIENTS: ALCOHOL 70 mL/100 mL
INACTIVE INGREDIENTS: Water; Glycerin; Polysorbate 20; CHAMAECYPARIS OBTUSA LEAF; LEMON OIL; TEA TREE OIL; Butylene Glycol; 1,2-Hexanediol

ACTIVE INGREDIENT

ALCOHOL 70% v/v

INACTIVE INGREDIENTS

Water, Glycerin, Polysorbate 20, Chamaecyparis Obtusa Leaf Extract, Citrus Limon (Lemon) Peel Oil, Melaleuca Alternifolia (Tea Tree) Leaf Oil, Butylene Glycol, 1,2-Hexanediol

PURPOSE

ANTISEPTIC

WARNINGS

For external use only. Flammable. Keep away from heat or flame
--------------------------------------------------------------------------------------------------------
Do not use
• in children less than 2 months of age
• on open skin wounds
--------------------------------------------------------------------------------------------------------
When using this product keep out of eyes, ears, and mouth. In case of contact with eyes, rinse eyes thoroughly with water.
--------------------------------------------------------------------------------------------------------
Stop use and ask a doctor if irritation or rash occurs. These may be signs of a serious condition.

KEEP OUT OF REACH OF CHILDREN

If swallowed, get medical help or contact a Poison Control Center right away.

Uses

• For hand washing to decrease bacteria on the skin.

Directions

• Spray enough product on hands to cover all surfaces. Rub hands together until dry.
• Supervise children in the use of this product.

Other information

• Store between 15℃ to 30℃ (59℉ to 86℉)
• Avoid freezing and excessive heat above 40℃ (104℉)